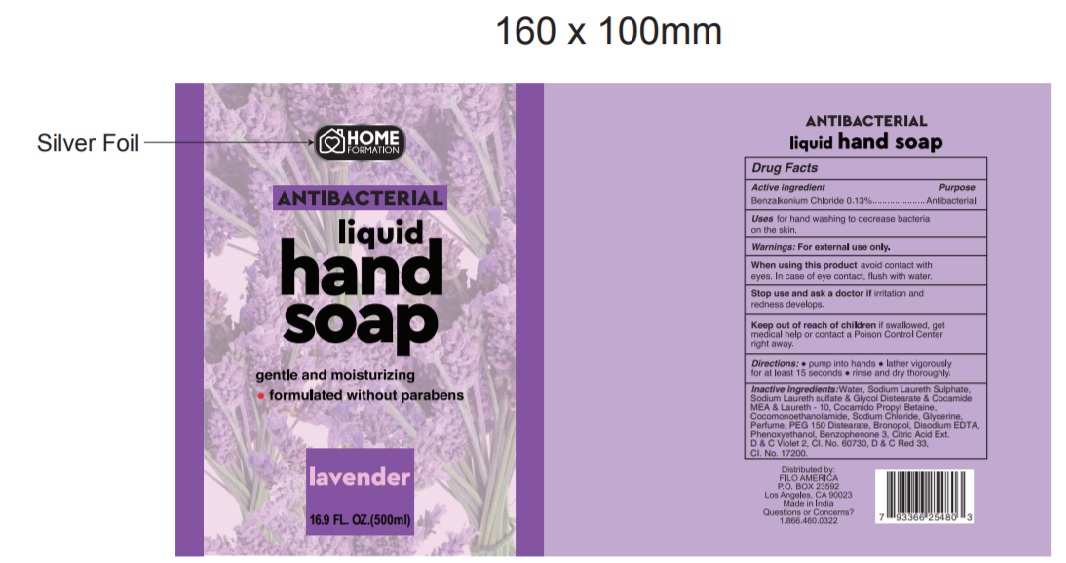 DRUG LABEL: Home formation Antibacterial Lavender
NDC: 68121-009 | Form: LIQUID
Manufacturer: PATCOS COSMETICS (INDIA) PRIVATE LIMITED
Category: otc | Type: HUMAN OTC DRUG LABEL
Date: 20210215

ACTIVE INGREDIENTS: BENZALKONIUM CHLORIDE 0.13 g/100 mL
INACTIVE INGREDIENTS: SODIUM CHLORIDE; GLYCERIN; SODIUM LAURETH SULFATE; COCAMIDOPROPYL BETAINE; COCO MONOETHANOLAMIDE; PEG-150 DISTEARATE; BRONOPOL; EDETATE DISODIUM ANHYDROUS; PHENOXYETHANOL; BENZOPHENONE; CITRIC ACID MONOHYDRATE; D&C RED NO. 33; WATER; D&C VIOLET NO. 2; CIFOSTODINE; LAURETH-10; GLYCOL DISTEARATE

Active ingredient

Benzalkonium Chloride (0.13%)

Purpose

Antibacterial

Warnings

For external use only.
When using this product avoid contact with eyes. In case of eyes contact, flush with water.

Stop use and ask a doctor if irritation and redness develops.

Keep out of reach of children if swallowed, get medical help or contact a Poison control center right away.

Uses

For hand washing to decrease bacteria on the skin.

Directions

• Pump into hands.
• Lather vigorously for at least 15 seconds.
• Rinse and dry thoroughly.

Inactive ingredient

Water, Sodium Laureth Sulphate,Sodium Laureth sulfate & Glycol Distearate & Cocamide MEA & Laureth - 10, Cocamido Propyl Betaine,
Cocomonoethanolamide, Sodium Chloride, Glycerine,Perfume, PEG 150 Distearate, Bronopol, Disodium EDTA,Phenoxyethanol, Benzophenone 3, Citric Acid ,D & C Violet 2, CI. No. 60730, D & C Red 33,CI. No. 17200.